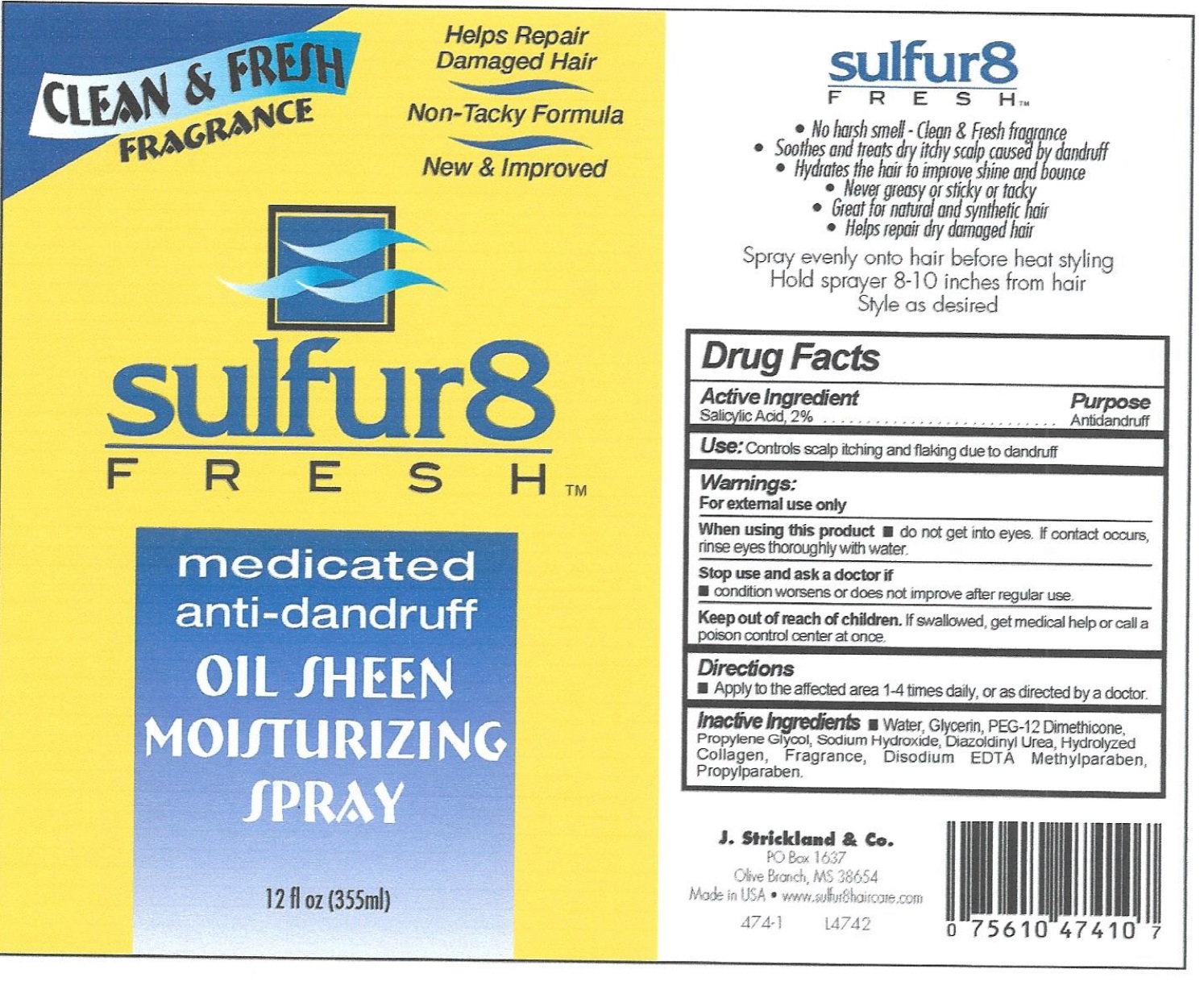 DRUG LABEL: Sulfur 8 Fresh Anti-Dandruff
NDC: 12022-028 | Form: SOLUTION
Manufacturer: J. Strickland & Co.
Category: otc | Type: HUMAN OTC DRUG LABEL
Date: 20231021

ACTIVE INGREDIENTS: SALICYLIC ACID 20 mg/1 mL
INACTIVE INGREDIENTS: WATER; GLYCERIN; PEG-12 DIMETHICONE; PROPYLENE GLYCOL; SODIUM HYDROXIDE; PROPYLPARABEN

Sulfur 8 Fresh Anti-Dandruff Spray

Active Ingredients

Salicylic Acid, 2%

Purpose

Antidandruff

Use:

Controls scalp itching and flaking due to dandruff

Warnings:

For external use only

When using this product

- do not get into eyes. If contact occurs, rinse eyes thoroughly with water.

Stop use and consult a doctor if

- condition worsens or does not improve after regular use

Keep out of reach of children

If swallowed, get medical help or call a poison control center at once.

Directions

- Apply to the affected area 1-4 times daily, or as directed by a doctor.

Inactive Ingredients

water, Mineral Oil, Aloe Barbadensis Leaf Juice, Isopropyl Myristate, Stearyl Alcohol, Ceteareth-20, Sodium Carbomer, Simmondsia Chinensis (Jojoba) Seed Oil, Hydrolyzed Collagen, Propylene Glycol, Tocopheryl Acetate, Methylparaben, Propylparaben, Diazolidinyl Urea, Sodium Lauryl Sulfate, Panthenol, Fragrance.